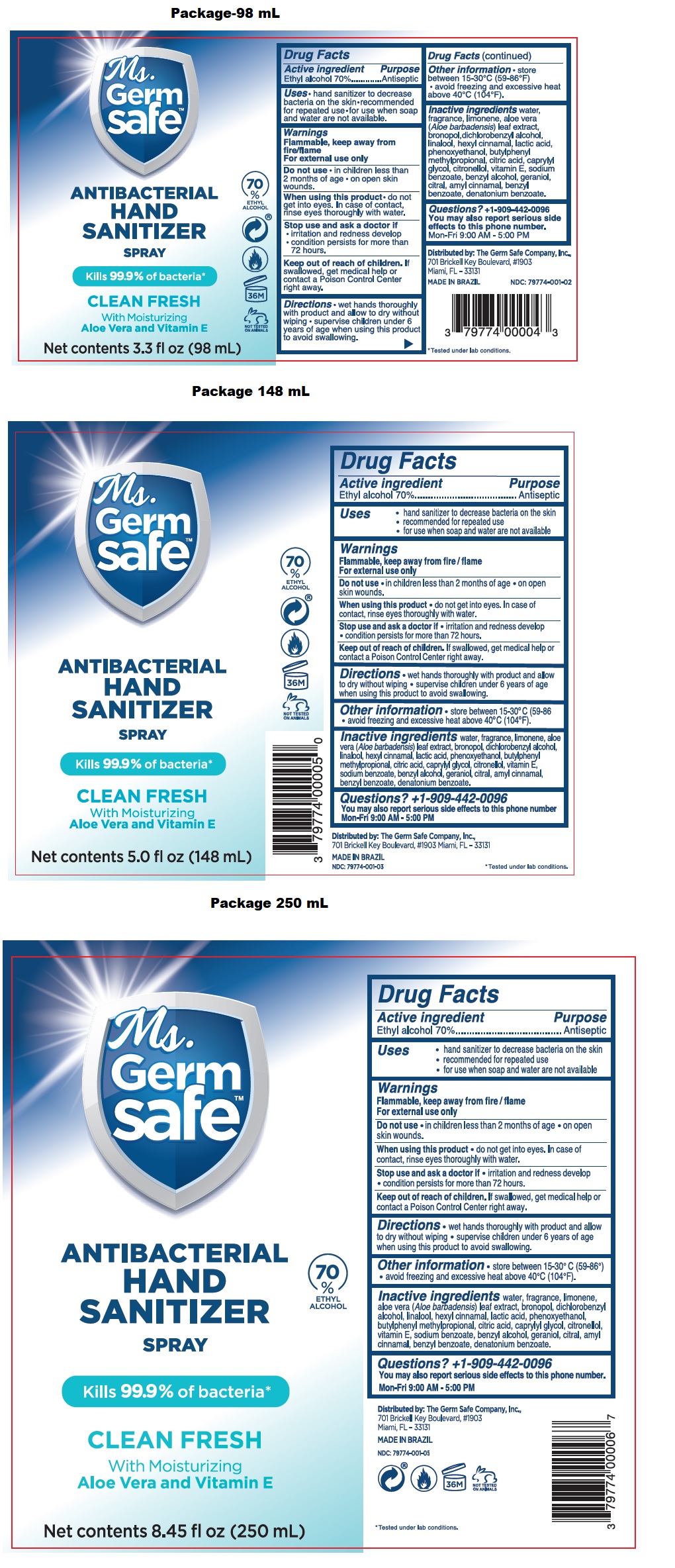 DRUG LABEL: Ms. Germsafe ANTIBACTERIAL HAND SANITIZER - CLEAN FRESH
NDC: 79774-001 | Form: SPRAY
Manufacturer: Germ Safe Company, Inc., The
Category: otc | Type: HUMAN OTC DRUG LABEL
Date: 20220127

ACTIVE INGREDIENTS: ALCOHOL 70 mL/100 mL
INACTIVE INGREDIENTS: WATER; LIMONENE, (+)-; ALOE VERA LEAF; BRONOPOL; DICHLOROBENZYL ALCOHOL; LINALOOL, (+/-)-; .ALPHA.-HEXYLCINNAMALDEHYDE; LACTIC ACID, UNSPECIFIED FORM; PHENOXYETHANOL; BUTYLPHENYL METHYLPROPIONAL; CITRIC ACID MONOHYDRATE; CAPRYLYL GLYCOL; .BETA.-CITRONELLOL, (R)-; .ALPHA.-TOCOPHEROL; SODIUM BENZOATE; BENZYL ALCOHOL; GERANIOL; CITRAL; .ALPHA.-AMYLCINNAMALDEHYDE; BENZYL BENZOATE; DENATONIUM BENZOATE

Ms. Germsafe™ ANTIBACTERIAL HAND SANITIZER SPRAY CLEAN FRESH

Active ingredient

Ethyl alcohol 70%

Purpose

Antiseptic

INDICATIONS AND USAGE

Uses • hand sanitizer to decrease bacteria on the skin

• recommended for repeated use

• for use when soap and water are not available

Warnings

Flammable, keep away from fire/flame

For external use only

Do not use • in children less than 2 months of age • on open skin wounds.

When using this product • do not get into eyes. In case of contact, rinse eyes thoroughly with water.

Stop use and ask a doctor if • irritation and redness develop • condition persists for more than 72hours.

Keep out of reach of children. If swallowed, get medical help or contact a Poison Control Center right away.

DOSAGE AND ADMINISTRATION

Directions • wet hands thoroughly with product and allow to dry without wiping • supervise children under 6 years of age when using this product to avoid swallowing.

Other information • store between 15-30°C (59-86°F) • avoid freezing and excessive heat above 40°C (104°F).

INACTIVE INGREDIENT

Inactive ingredients water, fragrance, limonene, aloe vera (Aloe barbadensis) leaf extract, bronopol, dichlorobenzyl alcohol, linalool, hexyl cinnamal, lactic acid, phenoxyethanol, butylphenyl methylpropional, citric acid, caprylyl glycol, citronellol, vitamin E, sodium benzoate, benzyl alcohol, geraniol, citral, amyl cinnamal, benzyl benzoate, denatonium benzoate.

Questions? +1-909-442-0096

You may also report serious side effects to this phone number.

Mon-Fri 9:00 AM - 5:00 PM

Kills 99.9% of bacteria*

With Moisturizing

Aloe Vera and Vitamin E

70% ETHYL ALCOHOL

NOT TESTED ON ANIMALS

Distributed by: The Germ Safe Company, Inc.,

701 Brickell Key Boulevard, #1903

Miami, FL - 33131

MADE IN BRAZIL

*Tested under lab conditions.